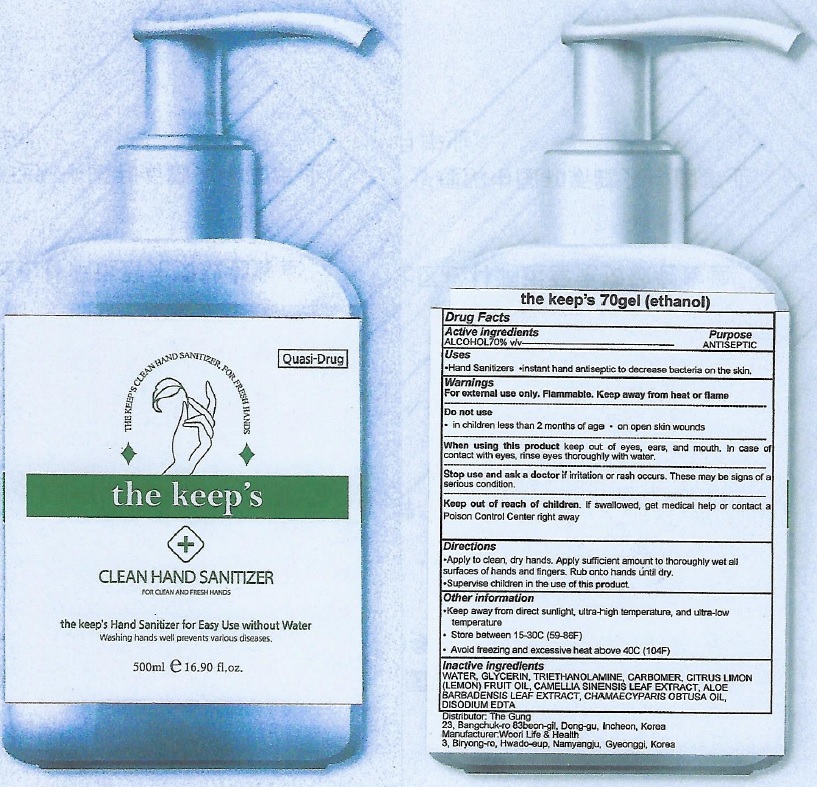 DRUG LABEL: the keeps 70 ETHANOL
NDC: 74710-0011 | Form: GEL
Manufacturer: THE GUNG CO LTD
Category: otc | Type: HUMAN OTC DRUG LABEL
Date: 20200707

ACTIVE INGREDIENTS: ALCOHOL 70 mL/100 mL
INACTIVE INGREDIENTS: WATER; GLYCERIN; TROLAMINE; CARBOMER HOMOPOLYMER, UNSPECIFIED TYPE; CITRUS X LIMON FRUIT OIL; GREEN TEA LEAF; ALOE VERA LEAF; CHAMAECYPARIS OBTUSA WOOD OIL; EDETATE DISODIUM ANHYDROUS

ACTIVE INGREDIENT

ALCOHOL 70% v/v

INACTIVE INGREDIENTS

WATER, GLYCERIN, TRIETHANOLAMINE, CARBOMER, CITRUS LIMON (LEMON) FRUIT OIL, CAMELLIA SINENSIS LEAF EXTRACT, ALOE BARBADENSIS LEAF EXTRACT, CHAMAECYPARIS OBTUSA OIL, DISODIUM EDTA

PURPOSE

ANTISEPTIC

WARNINGS

For external use only. Flammable. Keep away from heat or flame
--------------------------------------------------------------------------------------------------------
Do not use
• in children less than 2 months of age
• on open skin wounds
--------------------------------------------------------------------------------------------------------
When using this product keep out of eyes, ears, and mouth. In case of contact with eyes, rinse eyes thoroughly with water.
--------------------------------------------------------------------------------------------------------
Stop use and ask a doctor if irritation or rash occurs. These may be signs of a serious condition.

KEEP OUT OF REACH OF CHILDREN

If swallowed, get medical help or contact a Poison Control Center right away.

Uses

•Hand Sanitizers
•instant hand antiseptic to decrease bacteria on the skin.

Directions

• Apply to clean, dry hands. Apply sufficient amount to thoroughly wet all surfaces of hands and fingers. Rub onto hands until dry.
• Supervise children in the use of this product.

Other information

• Keep away from direct sunlight, ultra-high temperature, and ultra-low temperature
• Store between 15-30C (59-86F)
• Avoid freezing and excessive heat above 40C (104F)